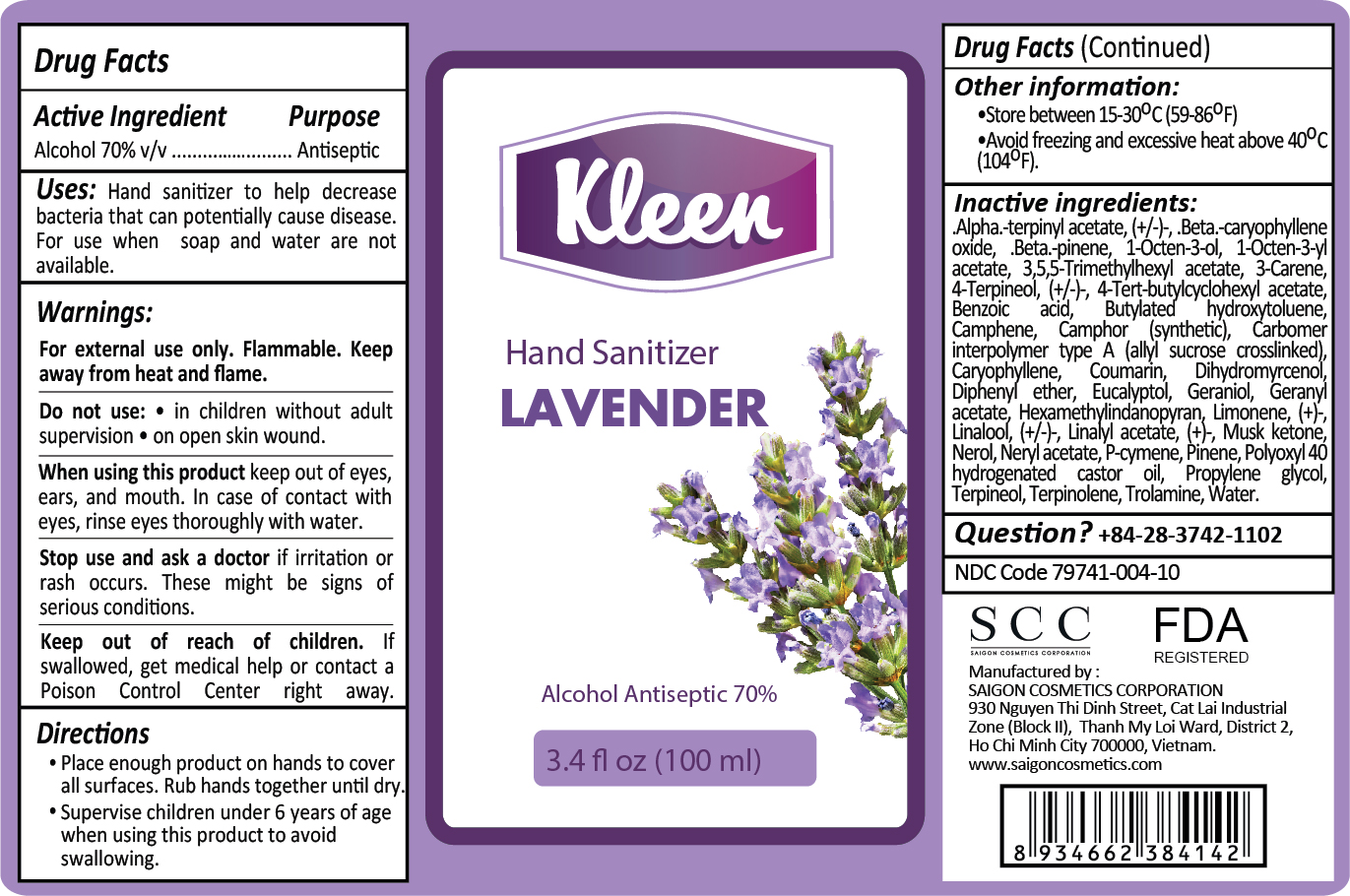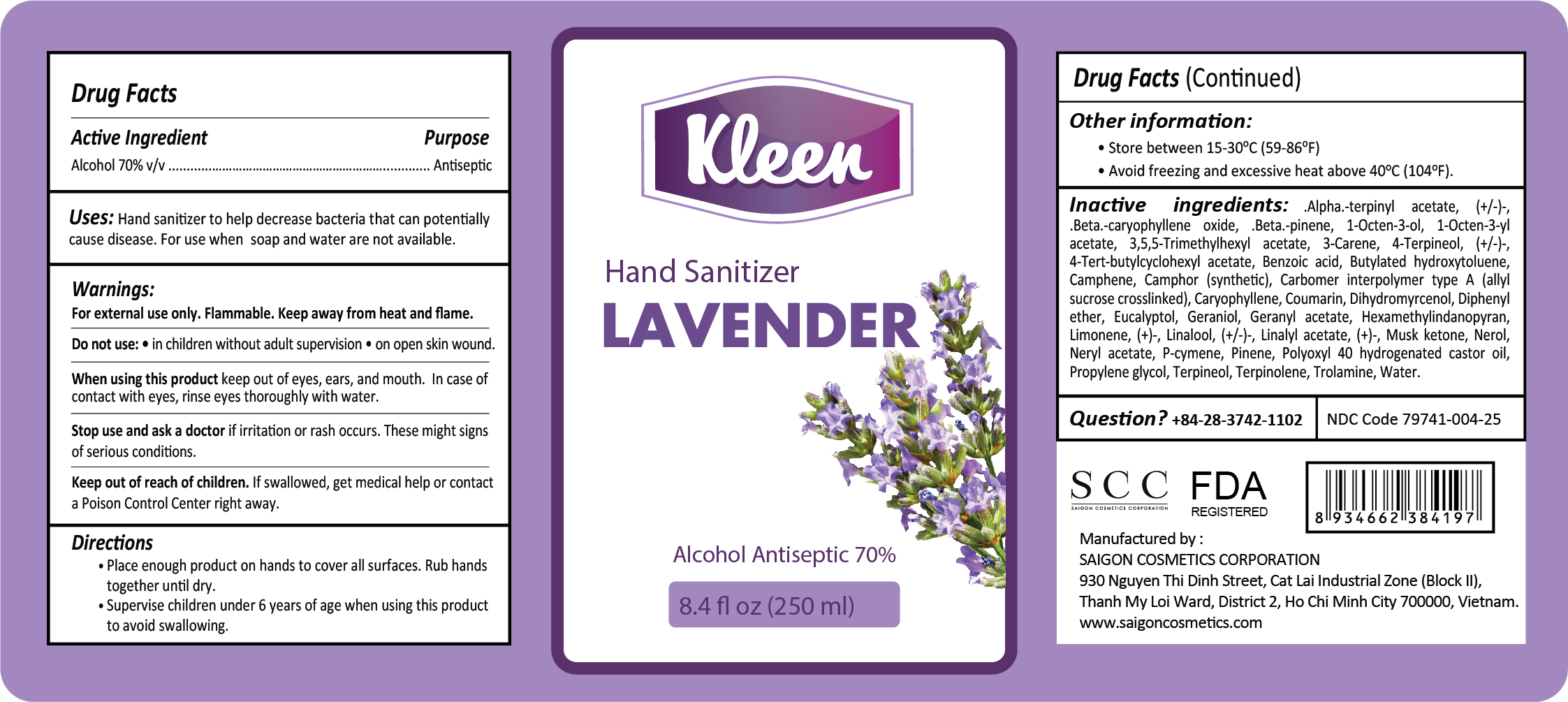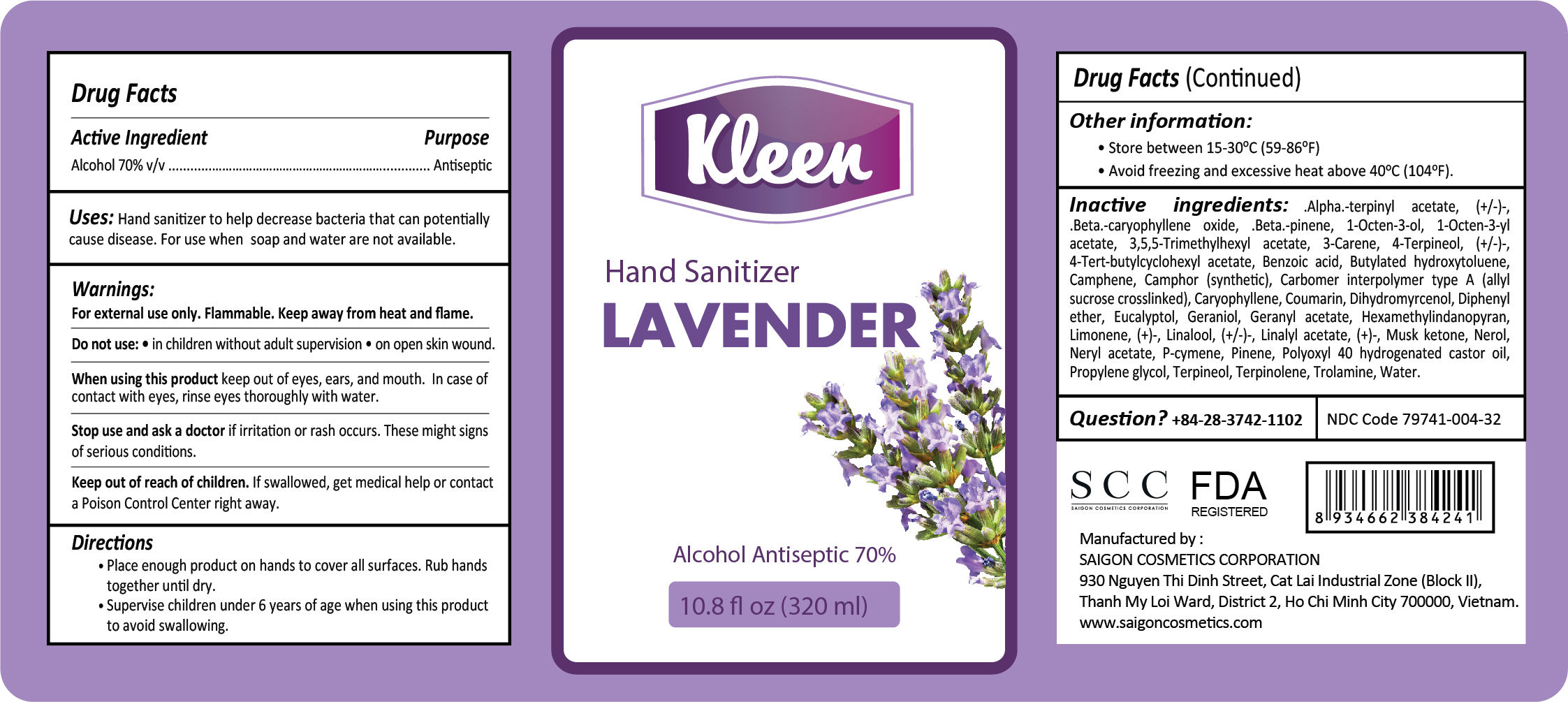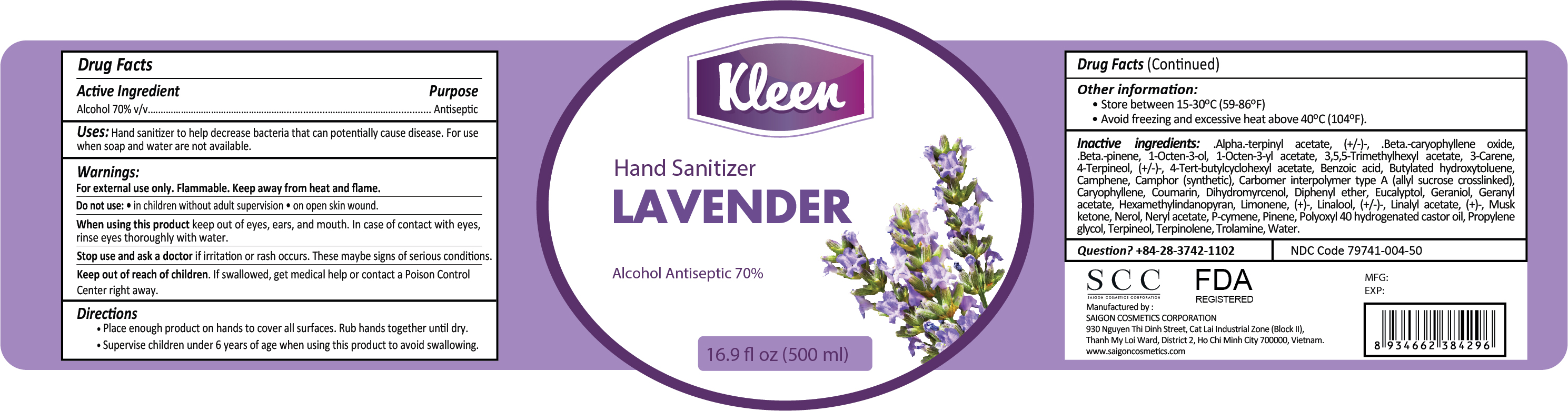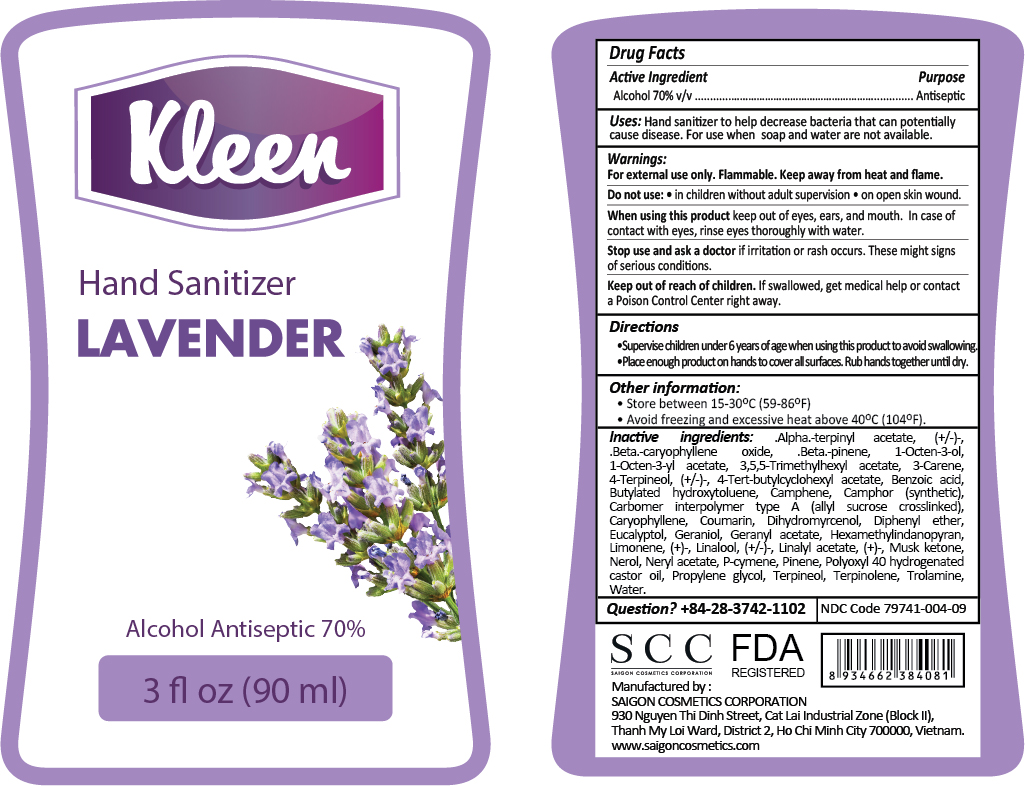 DRUG LABEL: KLEEN HAND SANITIZER RELAXING LAVENDER
NDC: 79741-004 | Form: GEL
Manufacturer: SAIGON COSMETICS CORPORATION
Category: otc | Type: HUMAN OTC DRUG LABEL
Date: 20200820

ACTIVE INGREDIENTS: ALCOHOL 70 mL/100 mL
INACTIVE INGREDIENTS: HEXAMETHYLINDANOPYRAN; 3-CARENE; .BETA.-CARYOPHYLLENE OXIDE; WATER; CAMPHENE; COUMARIN; CAMPHOR (SYNTHETIC); DIPHENYL ETHER; 4-TERPINEOL, (+/-)-; 4-TERT-BUTYLCYCLOHEXYL ACETATE; LIMONENE, (+)-; 1-OCTEN-3-YL ACETATE; .BETA.-PINENE; GERANYL ACETATE; TERPINOLENE; PINENE; CARBOMER INTERPOLYMER TYPE A (ALLYL SUCROSE CROSSLINKED); LINALYL ACETATE, (+)-; LINALOOL, (+/-)-; BUTYLATED HYDROXYTOLUENE; TROLAMINE; BENZOIC ACID; 1-OCTEN-3-OL; NEROL; NERYL ACETATE; P-CYMENE; .ALPHA.-TERPINYL ACETATE, (+/-)-; DIHYDROMYRCENOL; EUCALYPTOL; 3,5,5-TRIMETHYLHEXYL ACETATE; GERANIOL; MUSK KETONE; CARYOPHYLLENE; POLYOXYL 40 HYDROGENATED CASTOR OIL; PROPYLENE GLYCOL; TERPINEOL

ACTIVE INGREDIENT

Alcohol 70% v/v Purpose: Antiseptic

PURPOSE

Antiseptic, Hand Sanitizer

INDICATIONS AND USAGE

Hand sanitizer to help decrease bacteria that can potentially cause disease. For use when soap and water are not available.

WARNINGS

For external use only. Flammable. Keep away from heat and flame.

Do not use

- In children without aldult supervision
- On open skin wound

When using this product keep out of eyes, ears, and mouth. In case of contact with eyes, rinse eyes thoroughly with water.

Stop use and ask a doctor if irritation or rash occurs. These may be signs of serious conditions.

Directions:

· Place enough product on hands to cover all surfaces. Rub hands together until dry.

· Supervise children under 6 years of age when using this product to avoid swallowing.

Other information:

- Store between 15-25oC (59-77oF)
- Avoid freezing and excessive heat above 40oC (104oF)

INACTIVE INGREDIENT

.Alpha.-terpinyl acetate, (+/-)-, .Beta.-pinene, .Beta.-caryophyllene oxide, 1-Octen-3-ol, 1-Octen-3-yl acetate, 3,5,5-Trimethylhexyl acetate, 3-Carene, 4-Terpineol, (+/-)-,4-Tert-butylcyclohexyl acetate, Benzoic acid, Butylated hydroxytoluene, Camphene, Camphor (synthetic), Carbomer interpolymer type a (allyl sucrose crosslinked), Caryophyllene, Coumarin, Dihydromyrcenol, Diphenyl ether, Eucalyptol, Geraniol, Geranyl acetate, Hexamethylindanopyran, Limonene, (+)-, Linalool, (+/-)-, Linalyl acetate, (+)-,Musk ketone, Nerol, Neryl acetate, P-cymene, Pinene, Polyoxyl 40 hydrogenated castor oil, Propylene glycol, Terpineol, Terpinolene, Trolamine, Water.

QUESTIONS

+84-28-3742-1102

Keep out of reach of children. If swallowed, get medical help or contact a poison control center right away.